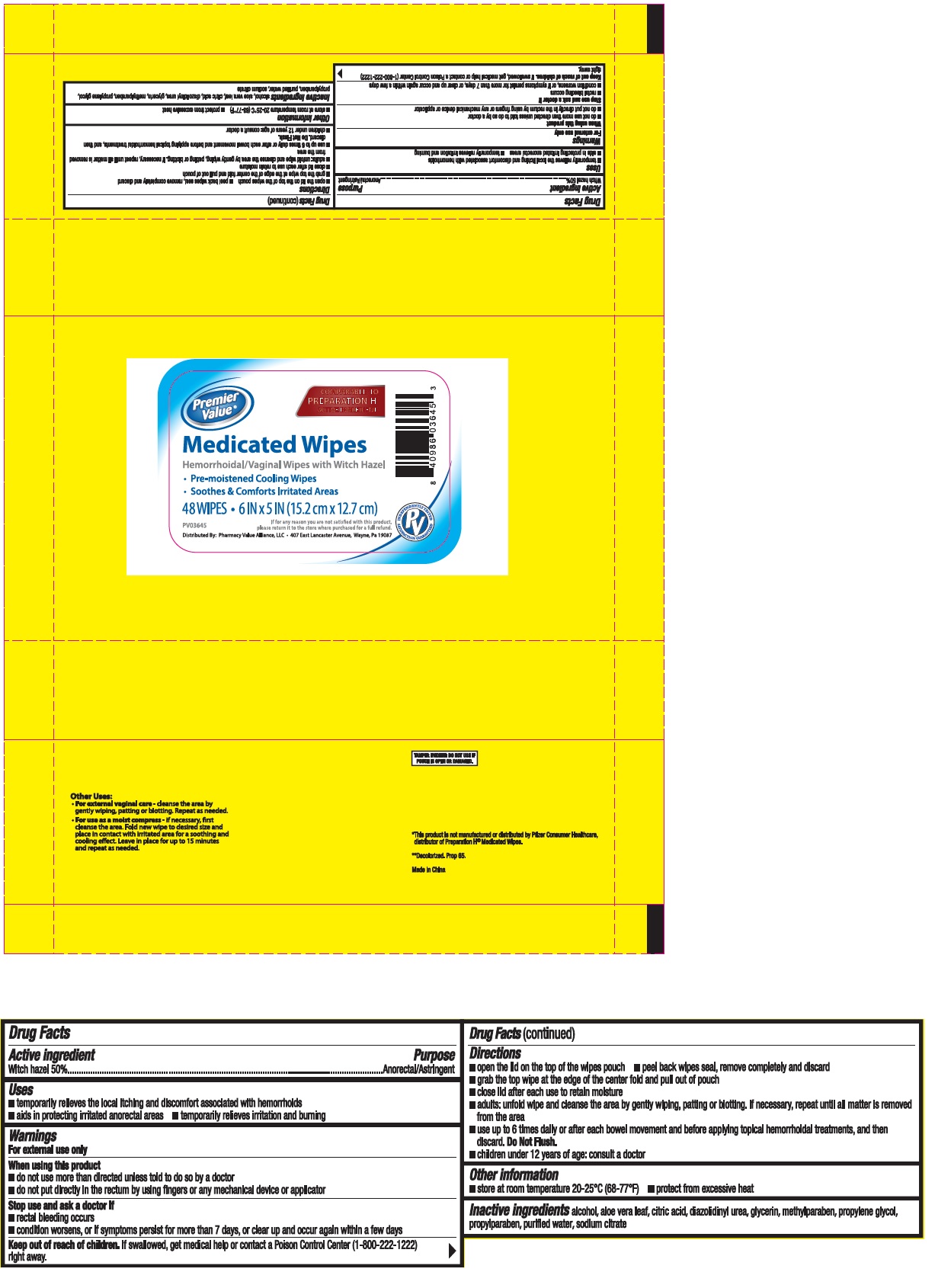 DRUG LABEL: Premier Value Medicated Wipes
NDC: 70108-028 | Form: CLOTH
Manufacturer: Ashtel Studios, Inc.
Category: otc | Type: HUMAN OTC DRUG LABEL
Date: 20230120

ACTIVE INGREDIENTS: WITCH HAZEL 0.02 g/1 1
INACTIVE INGREDIENTS: ALCOHOL; ALOE VERA LEAF; CITRIC ACID MONOHYDRATE; DIAZOLIDINYL UREA; GLYCERIN ; METHYLPARABEN; PROPYLENE GLYCOL; PROPYLPARABEN; WATER; SODIUM CITRATE, UNSPECIFIED FORM

Premier Value® Medicated Wipes

Active ingredient

Witch hazel 50%

Purpose

Anorectal/Astringent

Uses

• temporarily relieves the local itching and discomfort associated with hemorrhoids • aids in protecting irritated anorectal areas • temporarily relieves irritation and burning

Warnings

For external use only

When using this product

• do not use more than directed unless told to do so by a doctor

• do not put directly in the rectum by using fingers or any mechanical device or applicator

Stop use and ask a doctor if

• rectal bleeding occurs

• condition worsens, or if symptoms persist for more than 7 days, or clear up and occur again within a few days

Keep out of reach of children.

If swallowed get medical help or contact a Poison Control Centre (1-800-222-1222) right away.

Directions

• open the lid on the top of the wipes pouch

• peel back wipes seal, remove completely and discard

• grab the top wipe at the edge of the center fold and pull out of pouch

• close lid after each use to retain moisture

• adults: unfold wipe and cleanse the area by gently wiping, patting or blotting. If necessary, repeat until all matter is removed from the area

• use up to 6 times daily or after each bowel movement and before applying topical hemorroidal treatments, and then discard. Do Not Flush.

• children under 12 years of age: consult a doctor

Other information

• store at room temperature 20-25°C (68-77°F) • protect from excessive heat

Inactive ingredients

alcohol, aloe vera leaf, citric acid, diazolidinyl urea, glycerin, methylparaben, propylene glycol, propylparaben, purified water, sodium citrate

COMPARABLE TO PREPARATION H ACTIVE INGREDIENT

Hemorrhoidal/Vaginal Wipes with Witch Hazel

• Pre-moistened Cooling Wipes

• Soothes & Comforts Irritated Areas

• 6 IN x 5 IN (15.2 cm x 12.7 cm)

If for any reason you are not satisfied with this product, please return it to the store where purchased for a full refund.

Distributed By: Pharmacy Value Alliance, LLC • 407 East Lancaster Avenue, Wayne, Pa 19087

Other Uses:

• For external vaginal care - cleanse the area by gently wiping, patting or blotting. Repeat as needed.

• For use as a moist compress - if necessary, first cleanse the area. Fold new wipe to desired size and place in contact with irritated area for a soothing and cooling effect. Leave in place for up to 15 minutes and repeat as needed.

TAMPER EVIDENT: DO NOT USE IF POUCH IS OPEN OR DAMAGED.

*This product is not manufactured or distributed by Pfizer Consumer Healthcare, distributor of Preparation H® Medicated Wipes.

**Decolorized. Prop 65.

Made in China